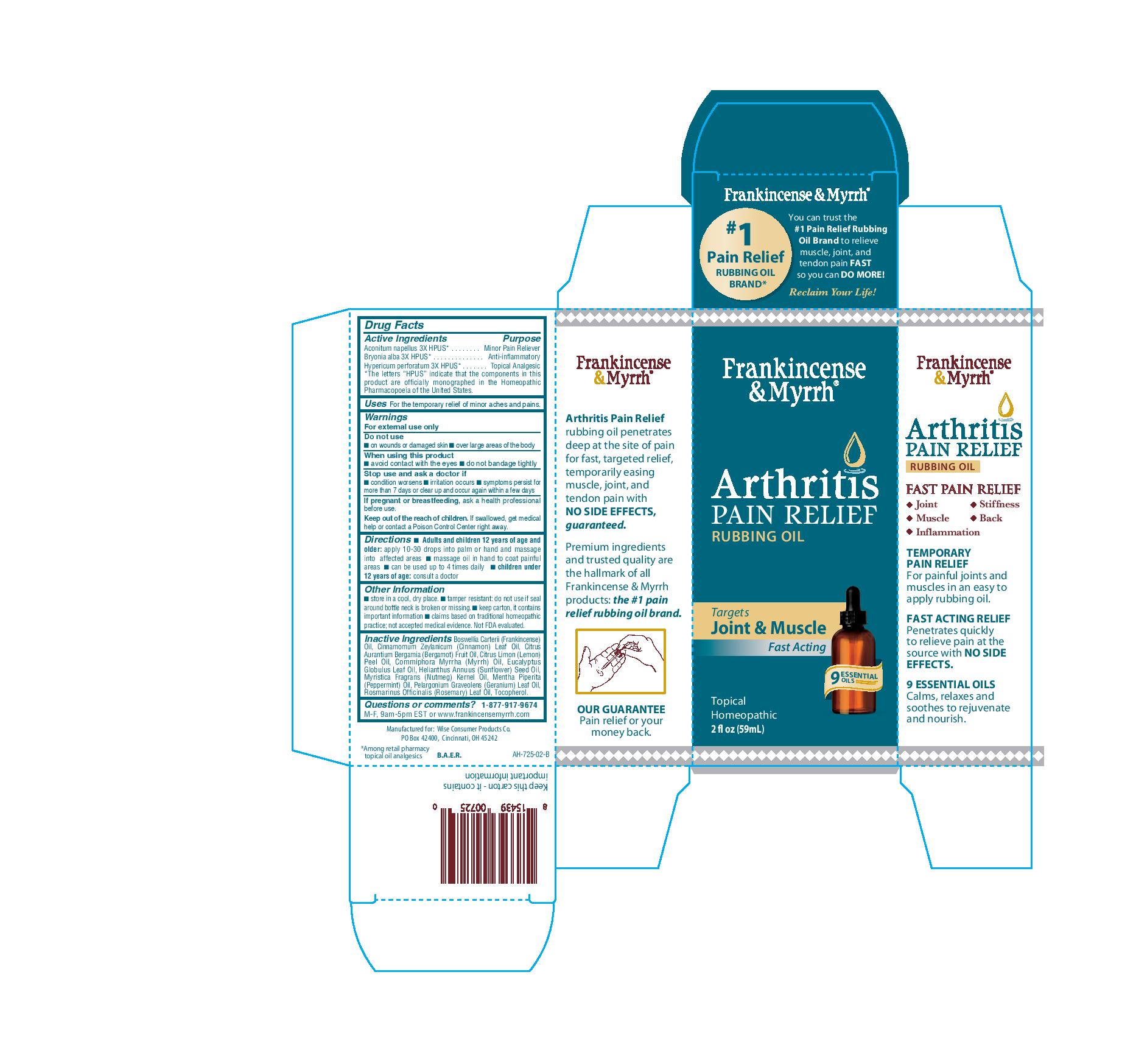 DRUG LABEL: Frankincense and Myrrh Arthritis Pain Relief
NDC: 42346-725 | Form: OIL
Manufacturer: Wise Consumer Products
Category: homeopathic | Type: HUMAN OTC DRUG LABEL
Date: 20251231

ACTIVE INGREDIENTS: ACONITUM NAPELLUS 3 [hp_X]/59 mL; BRYONIA ALBA ROOT 3 [hp_X]/59 mL; HYPERICUM PERFORATUM 3 [hp_X]/59 mL
INACTIVE INGREDIENTS: FRANKINCENSE OIL; BERGAMOT OIL; LEMON OIL; EUCALYPTUS GLOBULUS LEAF; SUNFLOWER OIL; PEPPERMINT OIL; GERANIUM OIL, ALGERIAN TYPE; ROSEMARY OIL; CINNAMON LEAF OIL; MYRRH OIL; NUTMEG OIL; TOCOPHEROL

Frankincense and Myrrh Arthritis Pain Relief Rubbing Oil

Active ingredients

Aconitum napellus 3X HPUS*

Bryonia alba 3X HPUS*

Hypericum perforatum 3X HPUS*

Purpose

Aconitum napellus 3X HPUS*.......................Minor Pain Reliever

Bryonia alba 3X HPUS*................................Anti-inflammatory

Hypericum perforatum 3X HPUS*................Topical Analgesic

*The letters "HPUS" indicate that the components in this product are officially monographed in the Homeopathic Pharmacopoeia of the United States.

Uses

For the temporary relief of minor aches and pains

Warnings

For external use only

Do not use

- on wounds or damaged skin
- over large areas of the body

When using this product

- avoid contact with the eyes
- do not bandage tightly

Stop use and ask a doctor if

- condition worsens
- irritation occurs
- symptoms persist for more than 7 days or clear up and occur again within a few days

PREGNANCY OR BREAST FEEDING

If pregnant or breastfeeding, ask a health professional before use.

Keep out of reach of children. If swallowed, get medical help or contact a Poison Control Center right away.

Directions

- Adults and children 12 years of age and older: apply 10-30 drops into palm or hand and massage into affected areas
- massage oil in hand to coat painful areas
- can be used up to 4 times daily
- children under 12 years of age: consult a physician

Other information

- store in a cool, dry place
- tamper resistant: do not use if seal around bottle neck is broken or missing
- keep carton, it contains important information
- claims based on traditional homeopathic practice; not accepted medical evidence. Not FDA evaluated.

Inactive ingredients

Boswellia Carterii (Frankincense) Oil, Cinnamomum Zeylanicum (Cinnamon) Leaf Oil, Citrus Aurantium Bergamia (Bergamot) Fruit Oil, Citrus Limon (Lemon) Peel Oil, Commiphora Myrrha (Myrrh) Oil, Eucalyptus Globulus Leaf Oil, Helianthus Annuus (Sunflower) Seed Oil, Myristica Fragrans (Nutmeg) Kernel Oil, Mentha Piperita (Peppermint) Oil, Pelargonium Graveolens (Geranium) Leaf Oil, Rosmarinus Officinalis (Rosemary) Leaf Oil, Tocopherol

Questions or comments?

1-877-917-9674 M-F, 9am-5pm EST or www.frankincensemyrrh.com

PACKAGE LABEL

Frankincense & Myrrh

Arthritis Pain Relief

Rubbing Oil

Targets Joint & Muscle

Fast Acting

9 Essential Oils

Homeopathic

2 fl oz (59mL)

NDC 42346-725-59